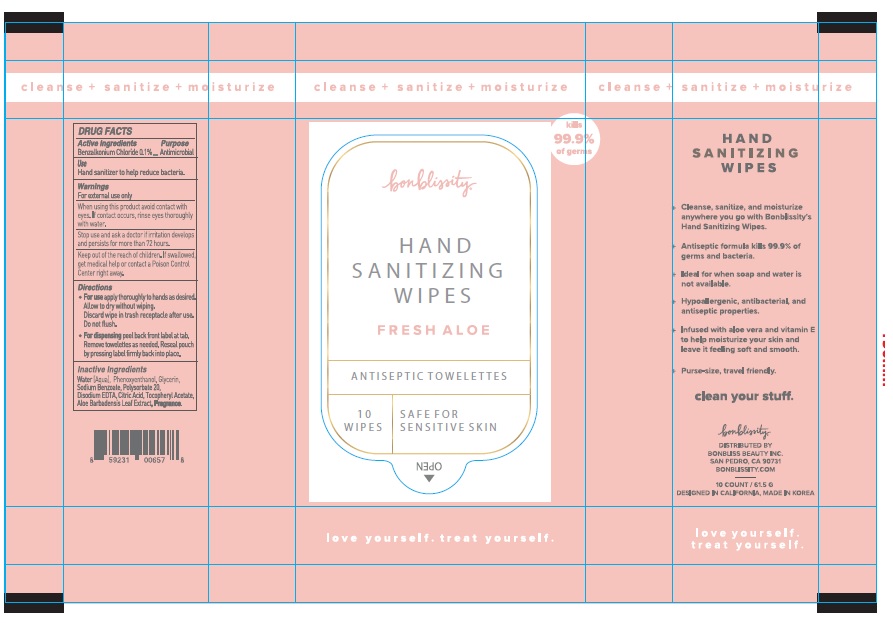 DRUG LABEL: BONBLISSITY HAND SANITIZING WIPES
NDC: 73582-0002 | Form: CLOTH
Manufacturer: BONBLISS BEAUTY, INC.
Category: otc | Type: HUMAN OTC DRUG LABEL
Date: 20230223

ACTIVE INGREDIENTS: BENZALKONIUM CHLORIDE 0.01 g/1 g
INACTIVE INGREDIENTS: WATER; PHENOXYETHANOL; GLYCERIN; SODIUM BENZOATE; POLYSORBATE 20; EDETATE DISODIUM ANHYDROUS; CITRIC ACID MONOHYDRATE; .ALPHA.-TOCOPHEROL ACETATE; ALOE VERA LEAF

73582-0002_BONBLISSITY HAND SANITIZING WIPES

Active ingredient

Benzalkonium Chloride 0.1%

Purpose

Antimicrobial

Use

- Hand sanitizer to help reduce bacteria

Warnings

For external use only

When using this product do not use in or near the eyes. If contact, rinse eyes thoroughly with water.

Stop use and ask a doctor if irritation develops and persists for more than 72 hours.

Keep out of reach of children. If swallowed, get medical help or contact a Poison Control Center right away.

Directions

For use apply thoroughly to hands as desired. Allow to dry without wiping. Discard wipe in trash receptacle after use. Do not flush.

For dispensing peel back front label at tab. Remove towelettes as needed. Reseal pouch by pressing label firmly back into place.

Inactive ingredients

Water, Phenoxyenthanol, Glycerin, Sodium Benzoate, Polysorbate 20, Disodium EDTA, Citric Acid, Tocopheryl Acetate, Aloe Barbadensis Leaf Extract, Fragrance